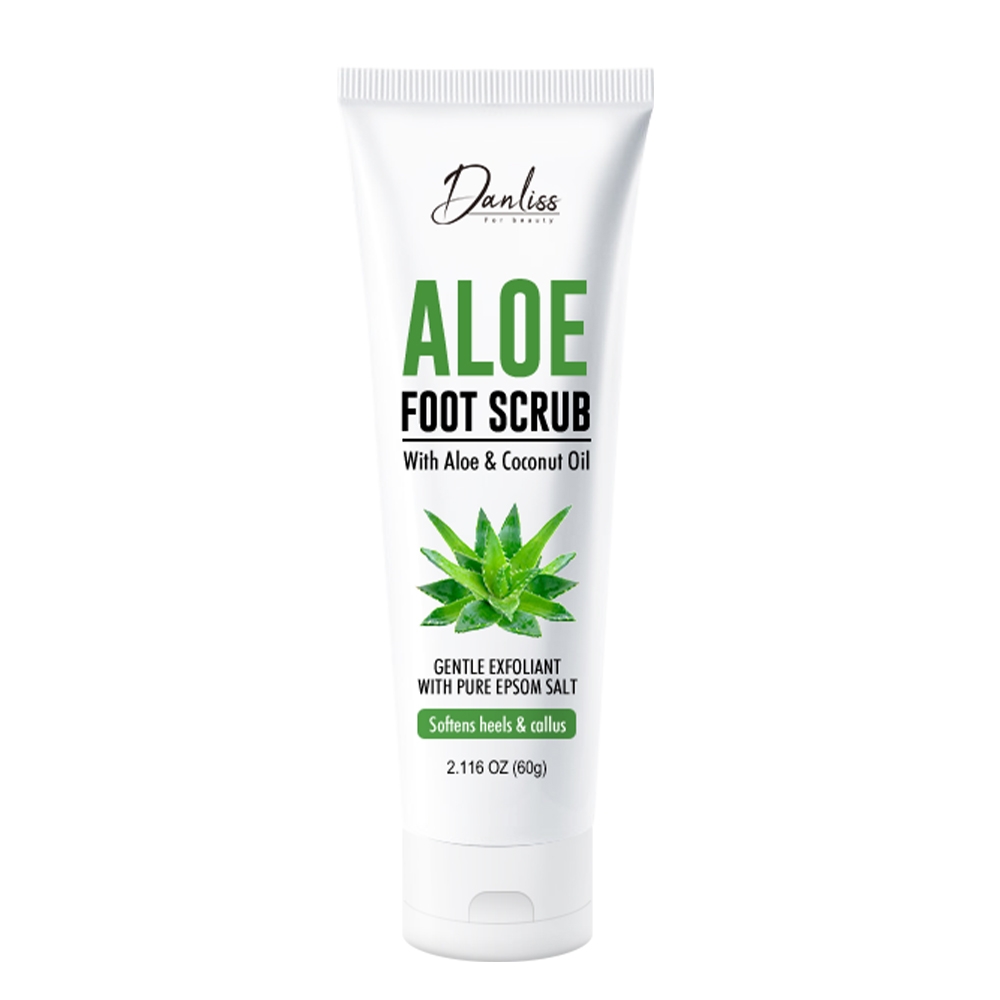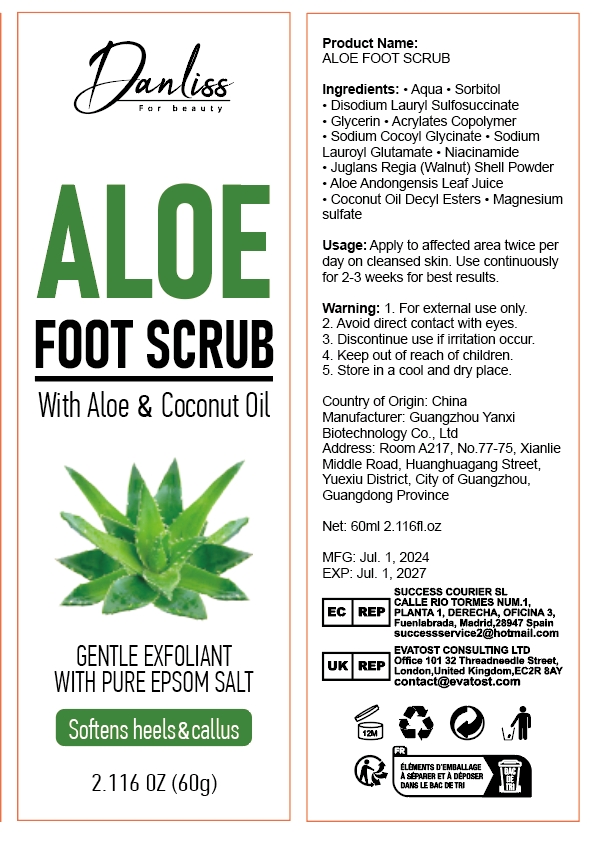 DRUG LABEL: Aloe foot scrub
NDC: 84025-149 | Form: CREAM
Manufacturer: Guangzhou Yanxi Biotechnology Co.. Ltd
Category: otc | Type: HUMAN OTC DRUG LABEL
Date: 20240815

ACTIVE INGREDIENTS: GLYCERIN 3 mg/60 g; MINERAL OIL 5 mg/60 g
INACTIVE INGREDIENTS: WATER

DOSAGE AND ADMINISTRATION

Scrub for moisturizing and caring for the skin on your feet

WARNINGS

Keep out of children

INACTIVE INGREDIENT

Aqua

INDICATIONS AND USAGE

For daily foot skin care

Keep out of children

PURPOSE

Moisturizing and cleansing foot skin